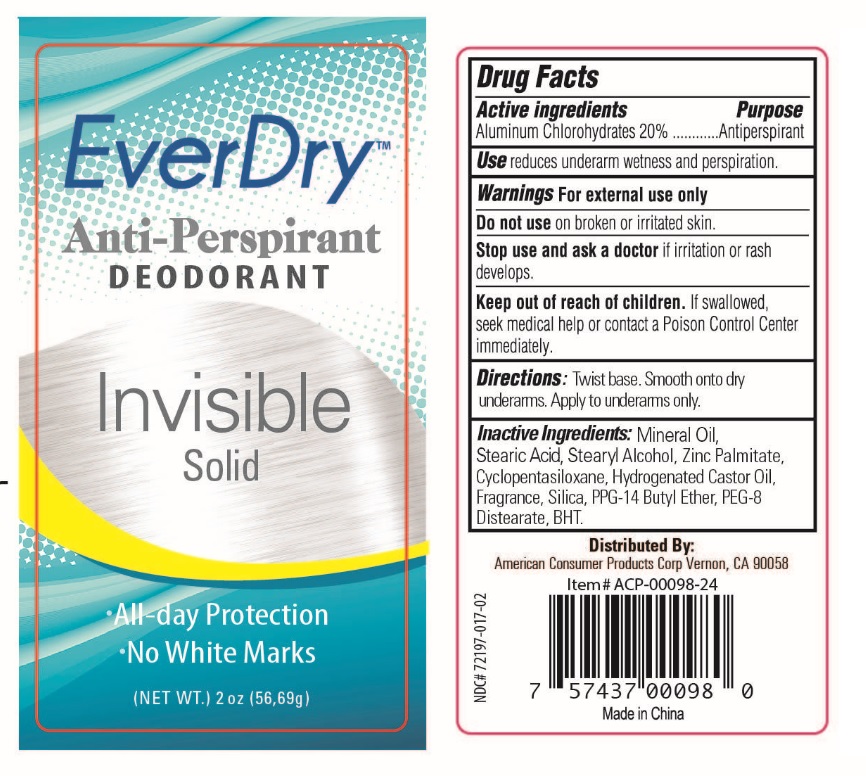 DRUG LABEL: 2.5OZ EverDry Antiperspirant Invisible
NDC: 72197-017 | Form: STICK
Manufacturer: American Consumer Products Corp
Category: otc | Type: HUMAN OTC DRUG LABEL
Date: 20250123

ACTIVE INGREDIENTS: ALUMINUM CHLOROHYDRATE 20 g/100 g
INACTIVE INGREDIENTS: ZINC PALMITATE; HYDROGENATED CASTOR OIL; BUTYLATED HYDROXYTOLUENE; PPG-14 BUTYL ETHER; MINERAL OIL; STEARIC ACID; STEARYL ALCOHOL; CYCLOMETHICONE 5; SILICON DIOXIDE; PEG-8 DISTEARATE

EverDry 2.5 OZ Anti Perspirant Invisible Solid

Active ingredients: Aluminum Chlorohydrate 20%

Purpose: Antiperspirant

Warnings: For external use only.

Keep out of reach of children. If swallowed, seek medical help or contact a Poison Control Center immediately.

INACTIVE INGREDIENT

Ingredients: Mineral Oil, Stearic Acid, Stearyl Alcohol, Zinc Palmitate, Cyclopentasiloxane, Hydrogenated Castor Oil, Fragrance, Silica, PPG-14 Butyl Ether, PEG-8 Disterate, BHT.

DOSAGE AND ADMINISTRATION

Directions: Twist base. Smooth onto dry underarms. Apply to underarms only.

Use: reduces underarm wetness and perspiration.

Stop use and ask a doctor if irritation or rash develops.

Do not use on broken or irritated skin.